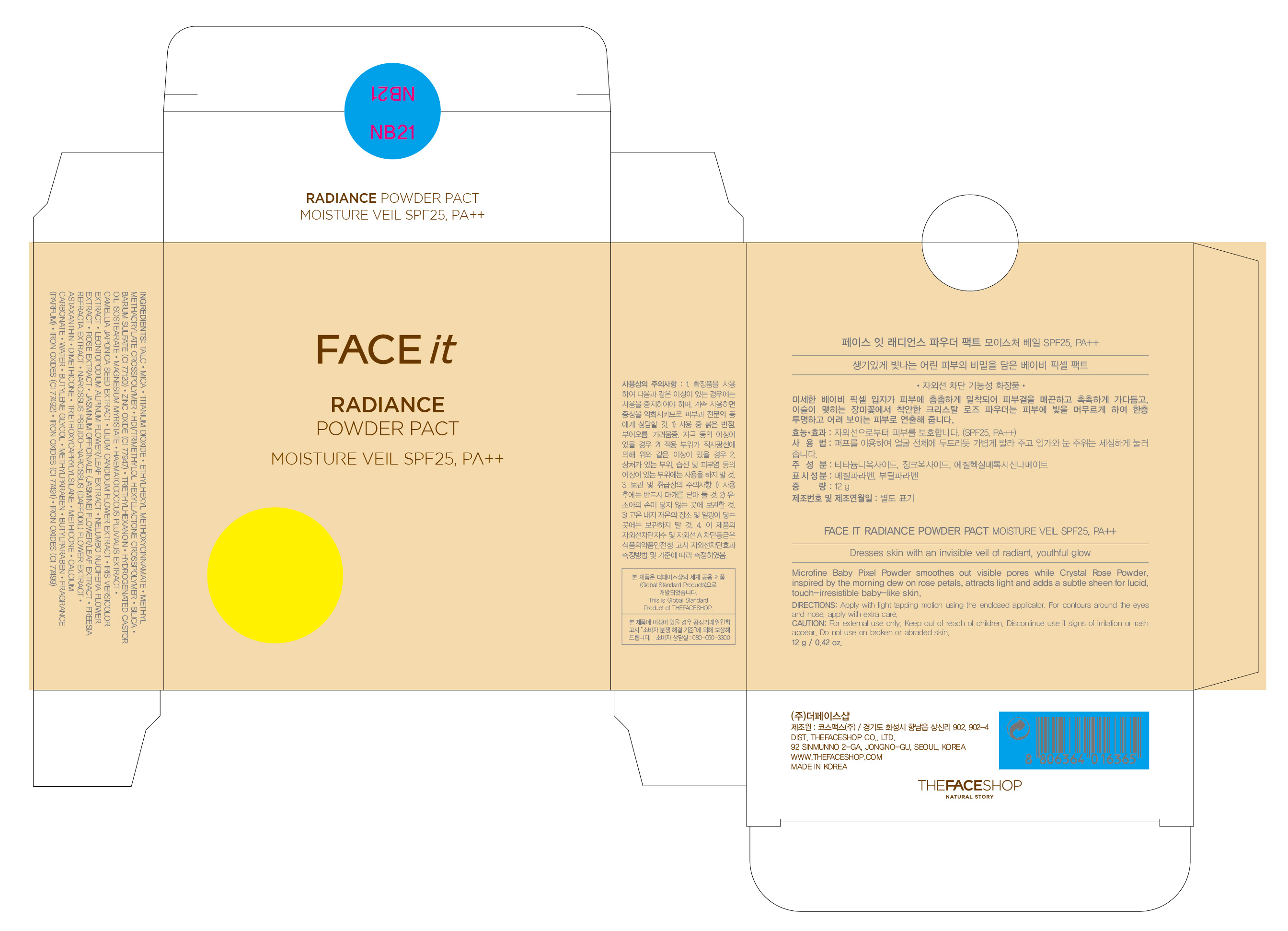 DRUG LABEL: FACE IT RADIANCE POWDER PACT SPF25 MOISTURE VEIL NB21
NDC: 51523-121 | Form: POWDER
Manufacturer: THEFACESHOP CO., LTD
Category: otc | Type: HUMAN OTC DRUG LABEL
Date: 20110913

ACTIVE INGREDIENTS: OCTINOXATE 4 g/100 g; TITANIUM DIOXIDE 6.208 g/100 g; ZINC OXIDE 1.96 g/100 g
INACTIVE INGREDIENTS: WATER; TRIETHOXYCAPRYLYLSILANE; TALC; MICA; SILICON DIOXIDE; BARIUM SULFATE; TRIETHYLHEXANOIN; MAGNESIUM MYRISTATE; DIMETHICONE; FERRIC OXIDE YELLOW; METHYLPARABEN; FERRIC OXIDE RED; CALCIUM CARBONATE; BUTYLPARABEN; FERROSOFERRIC OXIDE; HAEMATOCOCCUS PLUVIALIS; BUTYLENE GLYCOL; ASTAXANTHIN; CAMELLIA JAPONICA SEED; LILIUM CANDIDUM FLOWER; LEONTOPODIUM ALPINUM FLOWERING TOP; NELUMBO NUCIFERA FLOWER; JASMINUM OFFICINALE FLOWER; NARCISSUS PSEUDONARCISSUS FLOWER

FACE IT RADIANCE POWDER PACT SPF25 MOISTURE VEIL NB21

ACTIVE INGREDIENT

OCTINOXATE (4%)
TITANIUM DIOXIDE (6.208%)
Zinc Oxide (1.96%)

INACTIVE INGREDIENT

WATER
TRIETHOXYCAPRYLYLSILANE
TALC
MICA
SILICON DIOXIDE
BARIUM SULFATE
TRIETHYLHEXANOIN
MAGNESIUM MYRISTATE
DIMETHICONE
FERRIC OXIDE YELLOW
METHYLPARABEN
FERRIC OXIDE RED
CALCIUM CARBONATE
BUTYLPARABEN
FERROSOFERRIC OXIDE
HAEMATOCOCCUS PLUVIALIS
BUTYLENE GLYCOL
ASTAXANTHIN
CAMELLIA JAPONICA SEED
LILIUM CANDIDUM FLOWER
LEONTOPODIUM ALPINUM FLOWERING TOP
NELUMBO NUCIFERA FLOWER
JASMINUM OFFICINALE FLOWER
NARCISSUS PSEUDONARCISSUS FLOWER

PURPOSE

Provides high protection against sunburn and tanning.

WHEN USING

Avoid contact with eyes.

STOP USE

Discontinue use if sign of irritation or rash appear.

DOSAGE AND ADMINISTRATION

Dispense an adequate amount and apply evenly. (At the final stage of basic skincare, dispense an adequate amount and apply evenly to desired parts)

PACKAGE LABEL

FACE IT RADIANCE POWDER PACT SPF25 MOISTURE VEIL NB21